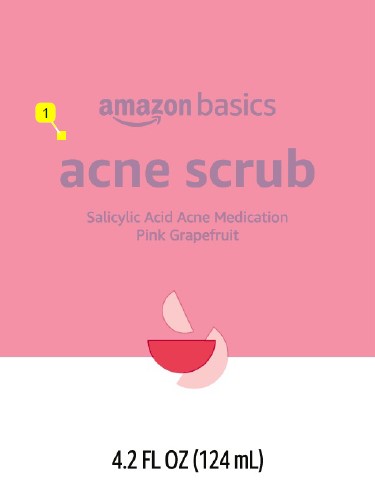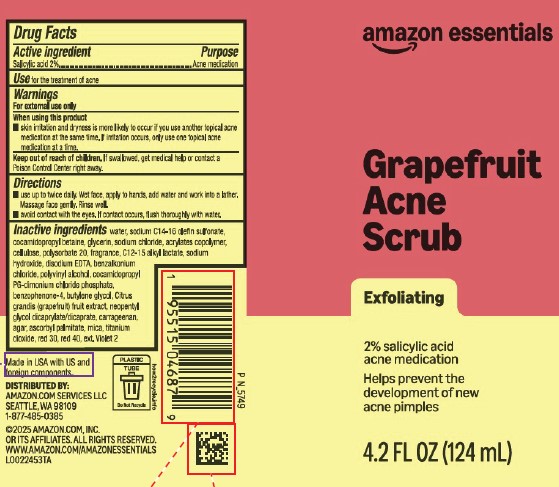 DRUG LABEL: Acne Scrub
NDC: 72288-821 | Form: GEL
Manufacturer: Amazon.com Services LLC
Category: otc | Type: HUMAN OTC DRUG LABEL
Date: 20260211

ACTIVE INGREDIENTS: SALICYLIC ACID 20 mg/1 mL
INACTIVE INGREDIENTS: WATER; SODIUM C14-16 OLEFIN SULFONATE; COCAMIDOPROPYL BETAINE; GLYCERIN; SODIUM CHLORIDE; BUTYL ACRYLATE/METHYL METHACRYLATE/METHACRYLIC ACID COPOLYMER (18000 MW); POWDERED CELLULOSE; POLYSORBATE 20; C12-15 ALKYL LACTATE; SODIUM HYDROXIDE; EDETATE DISODIUM; BENZALKONIUM CHLORIDE; POLYVINYL ALCOHOL, UNSPECIFIED; COCAMIDOPROPYL PROPYLENE GLYCOL-DIMONIUM CHLORIDE PHOSPHATE; SULISOBENZONE; BUTYLENE GLYCOL; PUMMELO; NEOPENTYL GLYCOL DICAPRYLATE/DICAPRATE; CARRAGEENAN; AGAR, UNSPECIFIED; ASCORBYL PALMITATE; MICA; TITANIUM DIOXIDE; D&C RED NO. 30; FD&C RED NO. 40; EXT. D&C VIOLET NO. 2

Solimo_Basics_Essentials 821.004/821AH-AI
Oil Free Acne Scrub Pink Grapefruit

Active ingredient

Salicylic acid 2%

Purpose

Acne Medication

Use

For the treatment of acne

Warnings

For external use only

When using this product

- skin irritation and dryness is more likely to occur if you use another topical acne medication at the same time. If irritation occurs, only use one topical acne medication at a time

Keep out of reach of children.

If swallowed, get medical help or contact a Poison Control Center right away.

Directions

- use up to twice daily. Wet face, apply to hands, add water and work into a lather. Massage face gently. Rinse well.
- avoid contact with the eyes. If contact occurs, flush thoroughly with water.

Inactive ingredients

water, sodium C14-16 olefin sulfonate, cocamidopropyl betaine, glycerin, sodium chloride, acrylates copolymer, cellulose, polysorbate 20, fragrance, C12-15 alkyl lactate, sodium hydroxide, disodium EDTA, benzalkonium chloride, polyvinyl alcohol, cocamidopropyl PG-dimonium chloride phosphate, benzophenone-4, butylene glycol, Citrus grandis (grapefruit) fruit extract, neopentyl glycol dicaprylate/dicaprate, carrageenan, agar, ascorbyl palmitate, mica, titanium dioxide, red 30, red 40, ext Violet 2

ADVERSE REACTIONS

Made in USA with US and foreign components.

DISTRIBUTED BY:

Amazon.com Services, LLC

Seattle, WA 98109

1-877-485-0385

©2025 Amazon.com, Inc. or its affiliates. All rights reserved.

www.amazon.com/amazonessentials

PLASTIC TUBE

Do Not Recycle

how2recycle.info

Principal Display Panel

amazone essentials

Grapefruit Acne Scrub

Exfoliating

2% salicylic acid acne medication

Helps prevent the development of new acne pimples

4.2 FL OZ (124 mL)

principal display panel

amazon basics

Acne Scrub

SALICYLIC ACID ACNE MEDICATION

Pink Grapefruit

4.2 FL OZ (124 mL)